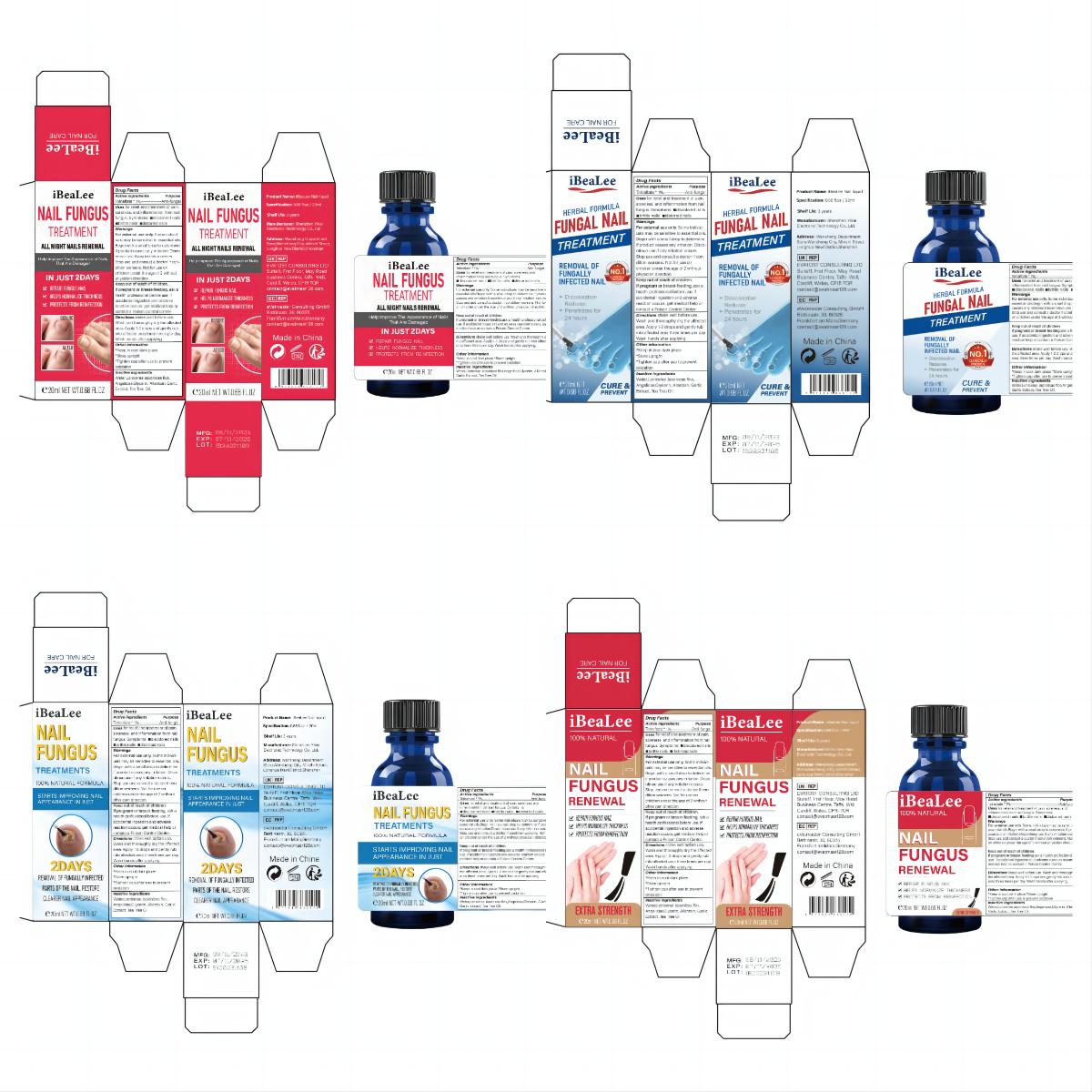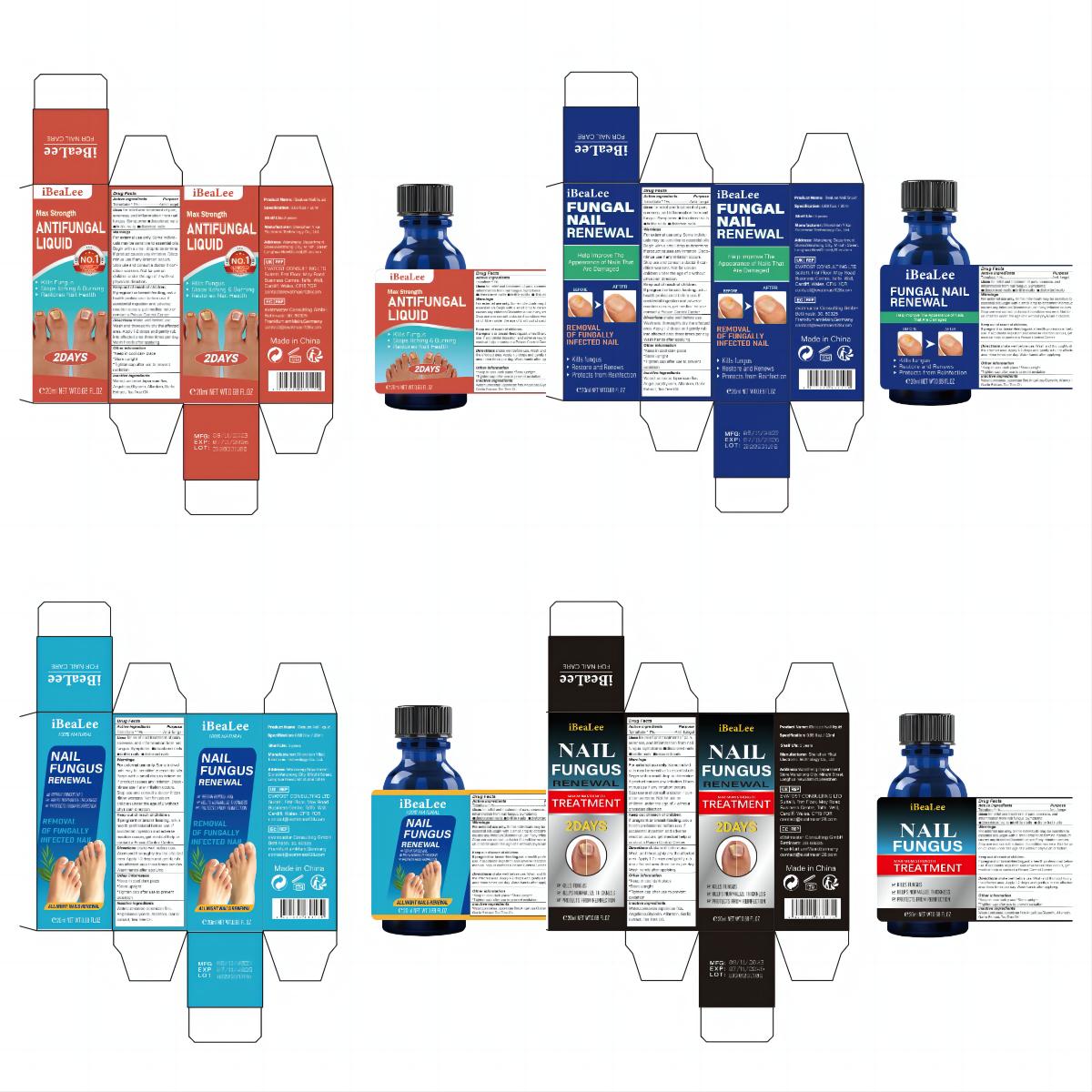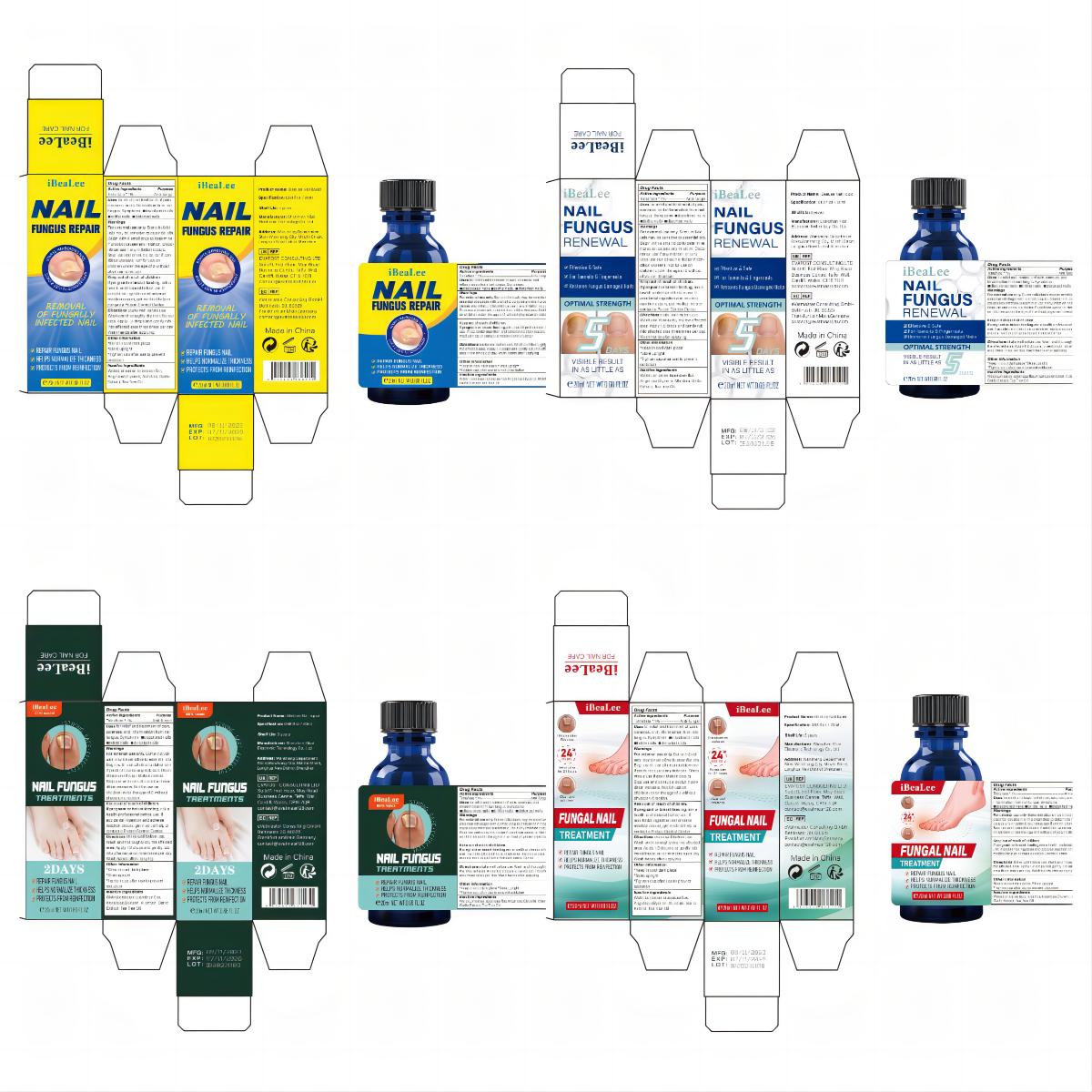 DRUG LABEL: iBeaLee Nali liquid
NDC: 83675-029 | Form: LIQUID
Manufacturer: Guangzhou Hanhai Trading Co., Ltd
Category: otc | Type: HUMAN OTC DRUG LABEL
Date: 20231112

ACTIVE INGREDIENTS: TOLNAFTATE 1 g/100 mL
INACTIVE INGREDIENTS: WATER; GLYCERIN; GARLIC; ALLANTOIN; TEA TREE OIL; LONICERA JAPONICA FLOWER; ANGELICA SINENSIS ROOT

Active Ingredient

Tolnaftate 1%

Purpose

Anti-fungal

Use

for relief and treatment of pain,
soreness, and inflammation from nail
fungus. Symptoms:

■discolored nails
■brittle nails

■distorted nails

Warnings

For external use only. Some individuals may be sensitive to essential oils. Begin with a small drop to determine if product causes any irritation. Discontinue use if any irritation occurs. Stop use and consult a doctor if condition worsens. Not for use on children under the age of 2 without physician direction.

Do not use

If you feel uncomfortable, please stop using it

When Using

Use after cleansing skin

Ask Doctor

ask doctor in case of Sensitive Skin

Keep Oot Of Reach Of Children

If pregnant or breast-feeding, ask a
health professional before use. If
accidental ingestion and adverse
reaction occurs, get medical help or
contact a Poison Control Center.

Directions

shake well before use.
Wash and thoroughly dry the affected
area. Apply 1-2 drops and gently rub
into affected area three times per day.
Wash hands after applying.

Other information

*Keep in cool dark place
*Store upright
*Tighten cap after use to prevent
oxidation

Inactive ingredients

Water,Lonicerae Japonicae flos,Angelicae,Glycerin, Allantoin, Garlic Extract, Tea Tree Oil.